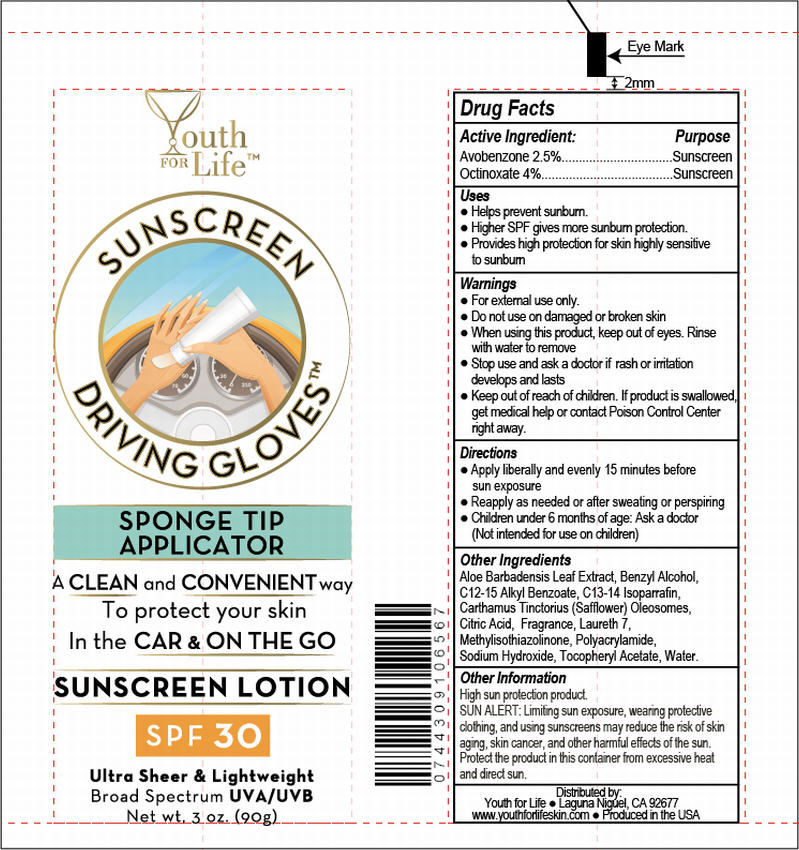 DRUG LABEL: Youth for Life SPF 30
NDC: 70555-007 | Form: LOTION
Manufacturer: Youth for Life
Category: otc | Type: HUMAN OTC DRUG LABEL
Date: 20160322

ACTIVE INGREDIENTS: Octinoxate 40 mg/1 g; Avobenzone 25 mg/1 g
INACTIVE INGREDIENTS: Aloe; Benzyl Alcohol; Carthamus Tinctorius Seed Oleosomes; Alkyl (C12-15) Benzoate; C13-14 Isoparaffin; Laureth-7; Methylisothiazolinone; Sodium Hydroxide; .Alpha.-Tocopherol Acetate; Water

Youth for Life™ SPF 30

Drug Facts

ACTIVE INGREDIENT

Active Ingredient: | Purpose
Avobenzone 2.5% | Sunscreen
Octinoxate 4% | Sunscreen

Uses

- Helps prevent sunburn
- Higher SPF gives more sunburn protection
- Provides high protection for skin highly sensitive to sunburn

Warnings

- For external use only

- Do not use on damaged or broken skin

- When using this product, keep out of eyes. Rinse with water to remove

- Stop use and ask a doctor if rash or irritation develops

- Keep out of reach of children. If product is swallowed, get medical help or contact Poison Control Center right away

Directions

- Apply liberally and evenly 15 minutes before sun exposure
- Reapply as needed or after sweating or perspiring
- Children under 6 months of age: Ask a doctor (Not intended for use on children)

Other Ingredients

Aloe Barbadensis Leaf Extract, Benzyl Alcohol, C12-15 Alkyl Benzoate, C13-14 Isoparrafin, Carthamus Tinctorius (Safflower) Oleosomes, Citric Acid, Fragrance, Laureth 7, Methylisothiazolinone, Polyacrylamide, Sodium Hydroxide, Tocopheryl Acetate, Water.

Other Information

High sun protection product.

SUN ALERT

Limiting sun exposure, wearing protective clothing, and using sunscreens may reduce the risk of skin aging, skin cancer, and other harmful effects of the sun. Protect the product in this container from excessive heat and direct sun.

Distributed by:
Youth for Life ● Laguna Niguel, CA 92677
www.youthforlifeskin.com ● Produced in the USA

PRINCIPAL DISPLAY PANEL - 90 g Tube Label

Youth
FOR Life™

SUNSCREEN
DRIVING GLOVES™

SPONGE TIP
APPLICATOR

A CLEAN and CONVENIENT way
To protect your skin
In the CAR & ON THE GO

SUNSCREEN LOTION

SPF 30

Ultra Sheer & Lightweight
Broad Spectrum UVA/UVB
Net wt. 3 oz. (90g)